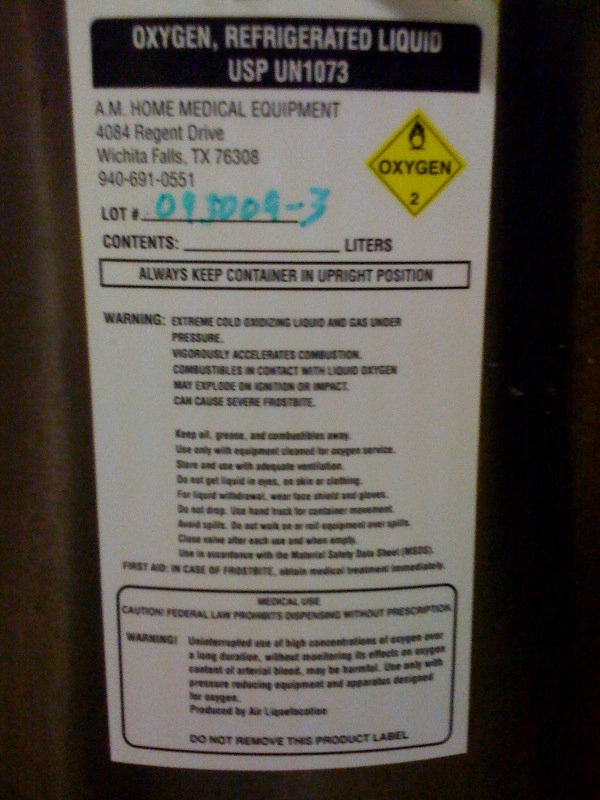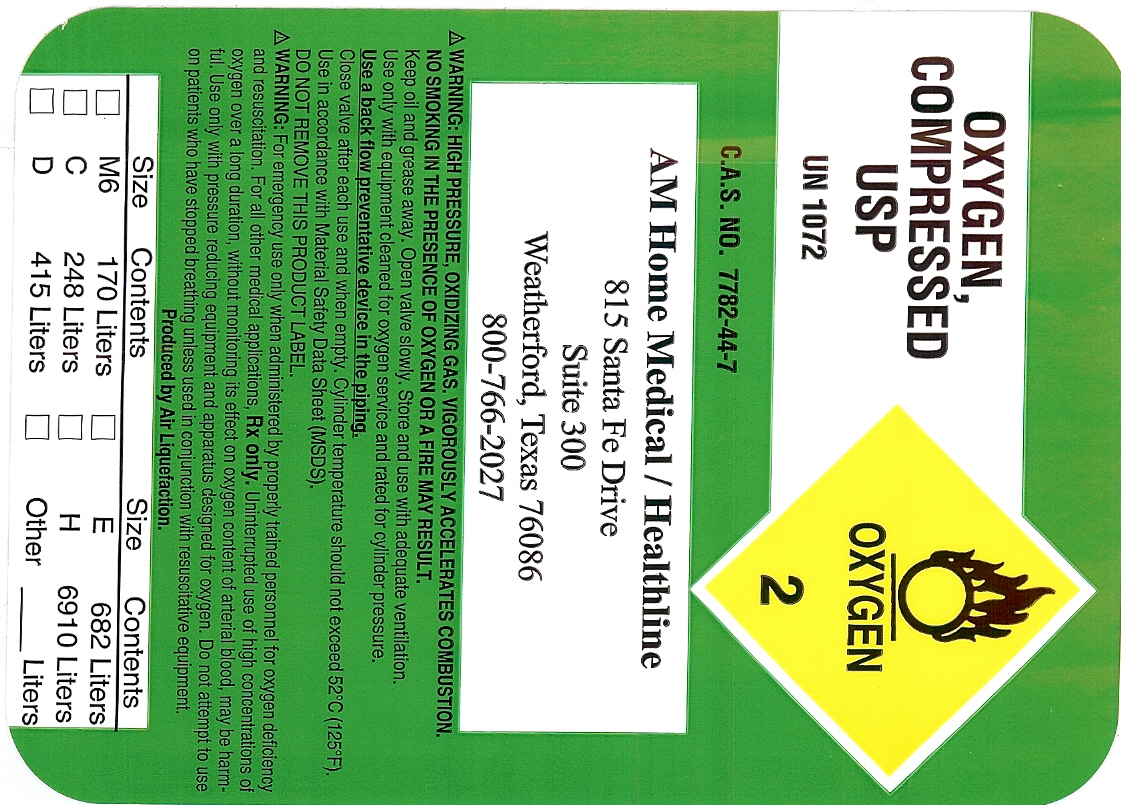 DRUG LABEL: Oxygen
NDC: 62149-0002 | Form: GAS
Manufacturer: A.M. Home Diagnostics Inc. dba Healthline
Category: prescription | Type: HUMAN PRESCRIPTION DRUG LABEL
Date: 20091026

ACTIVE INGREDIENTS: Oxygen 99 L/100 L

Oxygen